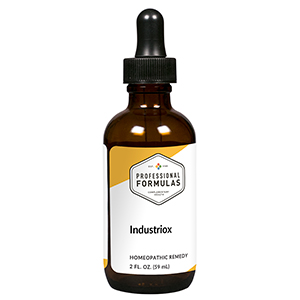 DRUG LABEL: Industriox
NDC: 63083-6011 | Form: LIQUID
Manufacturer: Professional Complementary Health Formulas
Category: homeopathic | Type: HUMAN OTC DRUG LABEL
Date: 20190815

ACTIVE INGREDIENTS: BERBERIS VULGARIS ROOT BARK 3 [hp_X]/59 mL; TARAXACUM OFFICINALE 3 [hp_X]/59 mL; AMMONIUM CATION 6 [hp_X]/59 mL; CAMPHOR (NATURAL) 6 [hp_X]/59 mL; STRYCHNOS NUX-VOMICA SEED 6 [hp_X]/59 mL; SULFURIC ACID 6 [hp_X]/59 mL; OYSTER SHELL CALCIUM CARBONATE, CRUDE 12 [hp_X]/59 mL; LACHESIS MUTA VENOM 12 [hp_X]/59 mL; LEAD 12 [hp_X]/59 mL; ACETONE 30 [hp_X]/59 mL; ACRYLIC ACID 30 [hp_X]/59 mL; BENZENE 30 [hp_X]/59 mL; CARBON TETRACHLORIDE 30 [hp_X]/59 mL; CHLOROFORM 30 [hp_X]/59 mL; METHYL ETHYL KETONE 30 [hp_X]/59 mL; FORMALDEHYDE SOLUTION 30 [hp_X]/59 mL; TERT-BUTYL METHYL ETHER 30 [hp_X]/59 mL; NAPHTHALENE 30 [hp_X]/59 mL; LIQUID PETROLEUM 30 [hp_X]/59 mL; TRICHLOROETHYLENE 30 [hp_X]/59 mL
INACTIVE INGREDIENTS: ALCOHOL; WATER

X11

ACTIVE INGREDIENTS

Berberis vulgaris 3X
Taraxacum officinale 3X
Ammonium carbonicum 6X
Camphora 6X
Nux vomica 6X
Sulphuricum acidum 6X, 12X
Calcarea carbonica 12X
Lachesis mutus 12X
Plumbum metallicum 12X
Acetonum 30X, 60X
Acrylic resins 30X, 60X
Benzinum 30X, 60X
Carboneum chloratum 30X, 60X
Chloroformum 30X, 60X
Ethylmethyl ketone 30X, 60X
Formalinum 30X, 60X
Gasoline (MTBE) 30X, 60X
Naphthalinum 30X, 60X
Petroleum 30X, 60X
Trichloroethylene 30X, 60X

QUESTIONS

Professional Formulas

PO Box 2034 Lake Oswego, OR 97035

INDICATIONS

For the temporary relief of fatigue, lethargy, headaches, muscle or joint pain, mild bloating or gas, disturbed sleep, or lack of concentration due to sensitivity to or exposure to industrial chemicals, paint, petroleum, steel, and plastics.*

PURPOSE

*Claims based on traditional homeopathic practice, not accepted medical evidence. Not FDA evaluated.

WARNINGS

In case of overdose, get medical help or contact a poison control center right away.

Keep out of the reach of children.

PREGNANCY OR BREAST FEEDING

If pregnant or breastfeeding, ask a healthcare professional before use.

DIRECTIONS

Place drops under tongue 30 minutes before/after meals. Adults and children 12 years and over: Take 10 drops up to 3 times per day. Consult a physician for use in children under 12 years of age.

OTHER INFORMATION

Tamper resistant. If seal is broken, do not use. After opening, close container tightly and store at room temperature away from heat.

INACTIVE INGREDIENTS

20% ethanol, purified water.

LABEL

Est 1985

Professional Formulas

Complementary Health

Industriox

Homeopathic Remedy

2 FL. OZ. (59 mL)